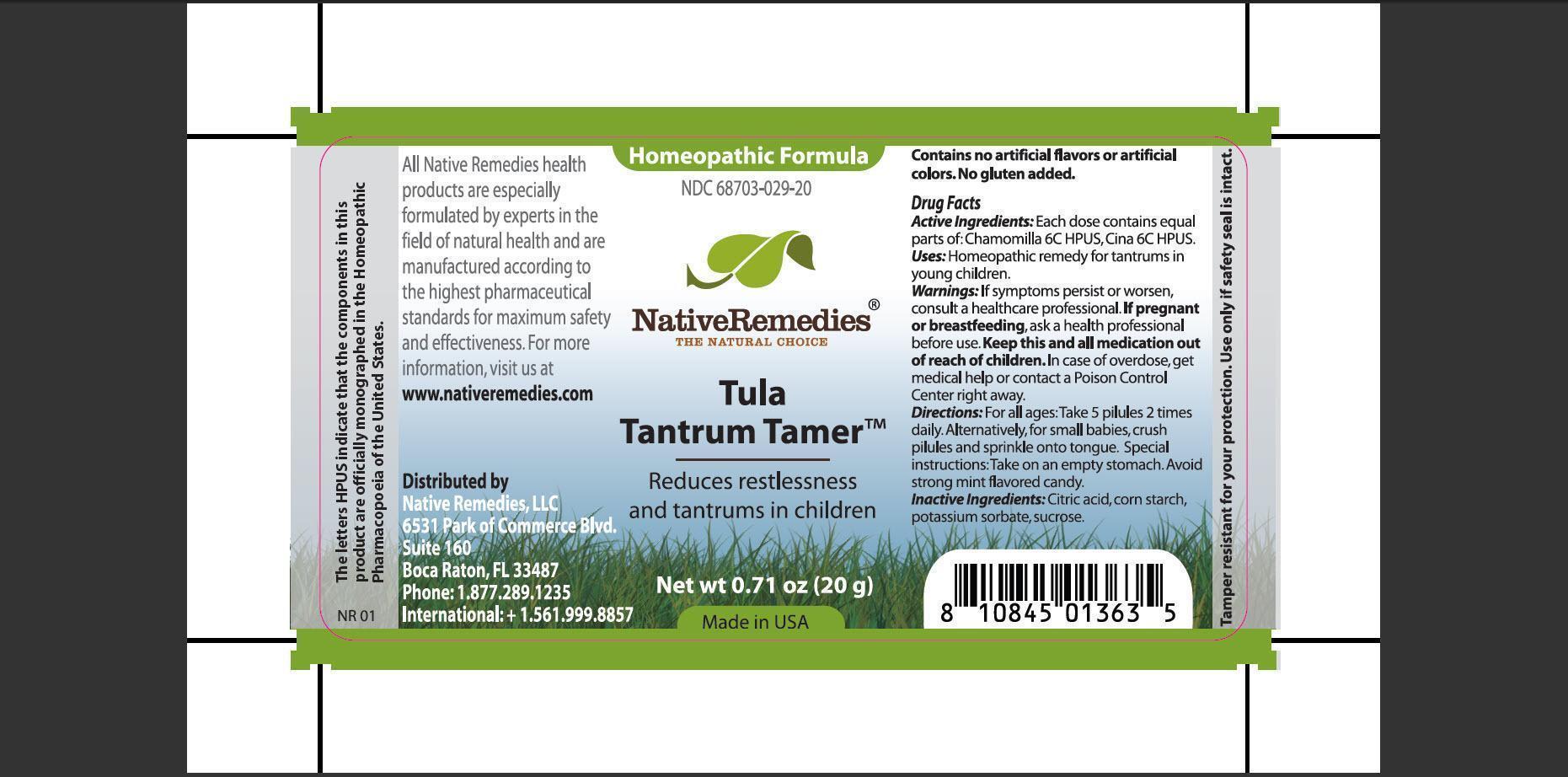 DRUG LABEL: Tula Tantrum Tamer
NDC: 68703-029 | Form: GRANULE
Manufacturer: Native Remedies, LLC
Category: homeopathic | Type: HUMAN OTC DRUG LABEL
Date: 20130130

ACTIVE INGREDIENTS: MATRICARIA RECUTITA 6 [hp_C]/50 mg; ARTEMISIA CINA PRE-FLOWERING TOP 6 [hp_C]/50 mg
INACTIVE INGREDIENTS: CITRIC ACID MONOHYDRATE; STARCH, CORN; POTASSIUM SORBATE; SUCROSE

Tula Tantrum Tamer

PURPOSE

Reduces restlessness and tantrums in children

ACTIVE INGREDIENT

Active Ingredients: Each dose contains equal parts of: Chamomilla 6C HPUS, Cina 6C HPUS

INDICATIONS AND USAGE

Uses: Homeopathic remedy for tantrums in young children

WARNINGS

Warnings: If symptoms persist or worsen, consult a healthcare professional

PREGNANCY OR BREAST FEEDING

If pregnant or breastfeeding, ask a health professional

KEEP OUT OF REACH OF CHILDREN

Keep this and all medication out of reach of children

OVERDOSAGE

In case of overdose, get medical help or contact a Poison Control Center right away

DOSAGE AND ADMINISTRATION

Directions: For all ages: Take 5 pilules 2 times daily. Alternatively, for small babies, crush pilules and sprinkle onto tongue. Special instruction: Take on an empty stomach. Avoid strong mint flavored candy

INACTIVE INGREDIENT

Inactive Ingredients:Citric acid, corn starch, potassium sorbate, sucrose

PATIENT COUNSELING INFORMATION

The letters HPUS indicate that the components in this product are officially monographed in the Homeopathic Pharmacopoeia of the United States.

All Native Remedies health products are especially formulated by experts in the field of natural health and are manufactures according to the highest pharmaceutical standards for maximum safety and effectiveness. For more information, visit us at www.nativeremedies.com

Distributed by
Native Remedies, LLC
6531 Park of Commerce Blvd.
Suite 160
Boca Raton, FL 33487
Phone:1.877.289.1235
International:+1.561.999.8857

Contains no artificial flavors or artificial colors. No gluten added.

STORAGE AND HANDLING

Tamper resistant for your protection. Use only if safety seal is intact.